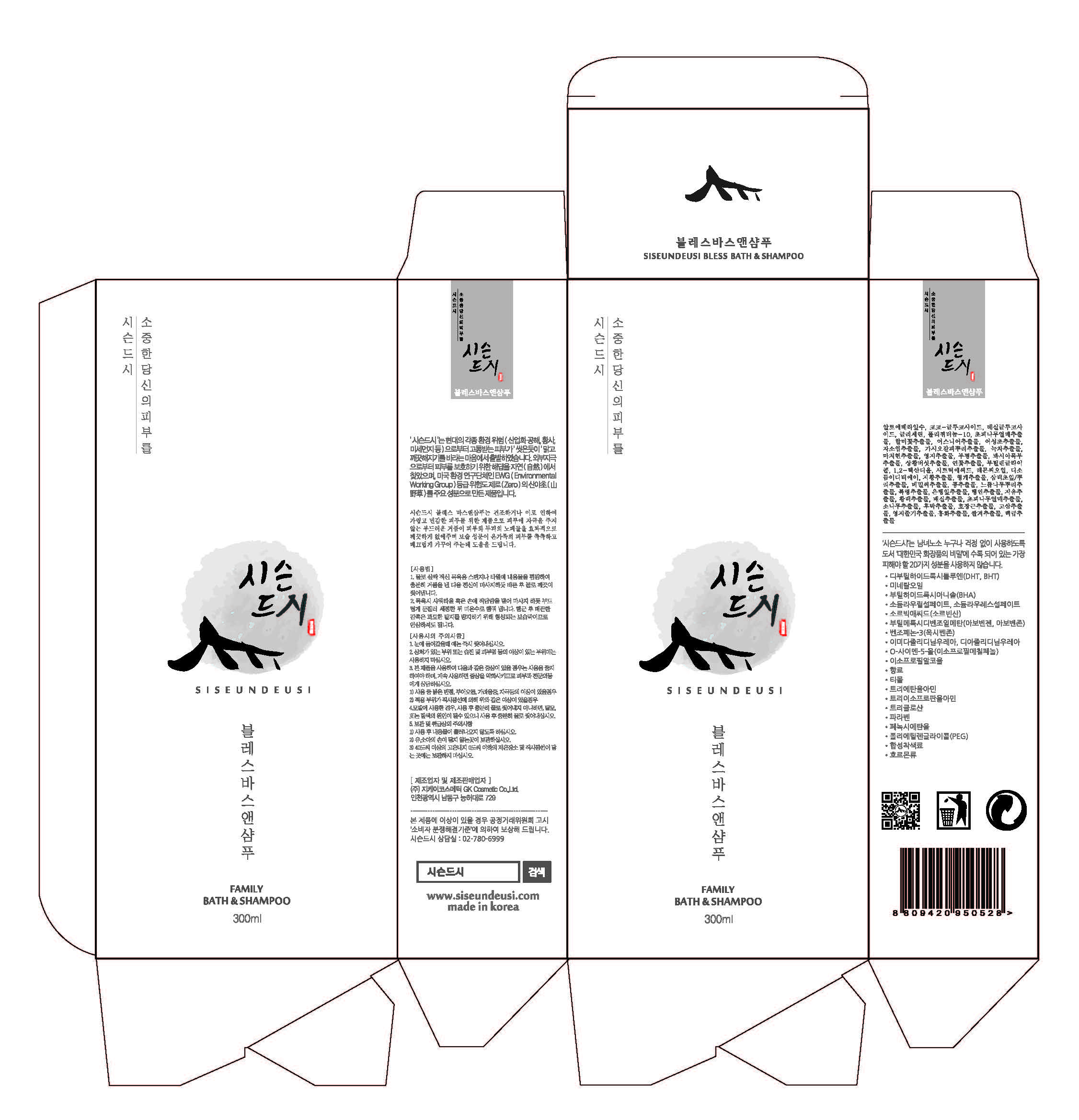 DRUG LABEL: SISEUNDEUSI BLESS BATHANDSHAMPOO
NDC: 70098-0007 | Form: GEL
Manufacturer: GK COSMETIC CO., LTD.
Category: otc | Type: HUMAN OTC DRUG LABEL
Date: 20170309

ACTIVE INGREDIENTS: GLYCERIN 2.661 g/100 mL
INACTIVE INGREDIENTS: BUTYLENE GLYCOL; ALOE VERA LEAF

Drug Facts

ACTIVE INGREDIENT

Glycerin

INACTIVE INGREDIENT

Aloe Barbadensis Leaf Water, Butylene Glycol, Etc

PURPOSE

Skin Protectant

keep out of reach of the children

INDICATIONS AND USAGE

1. Pump adequate amount of Bless Bath & Shampoo onto a wet sponge or washcloth and lather it with sponge or washcloth. Then gently rub your entire body, and rinse it all off
2. Pour adequate amount of Bless Bath & Shampoo on your hand or washcloth in the shower and gently rub your body and then rinse it all off with lukewarm water. Be relieved, smoothness after the wash off is generated moisture layer to avoid too much oil removal from the skin.

DOSAGE AND ADMINISTRATION

for external use only

WARNINGS

1. Do not use in the following cases(Eczema and scalp wounds)
2.Side Effects
1)Due to the use of this druf if rash, irritation, itching and symptopms of hypersnesitivity occur dicontinue use and consult your phamacisr or doctor
3.General Precautions
1)If in contact with the eyes, wash out thoroughty with water If the symptoms are servere, seek medical advice immediately
2)This product is for exeternal use only. Do not use for internal use
4.Storage and handling precautions
1)If possible, avoid direct sunlight and store in cool and area of low humidity
2)In order to maintain the quality of the product and avoid misuse
3)Avoid placing the product near fire and store out in reach of children